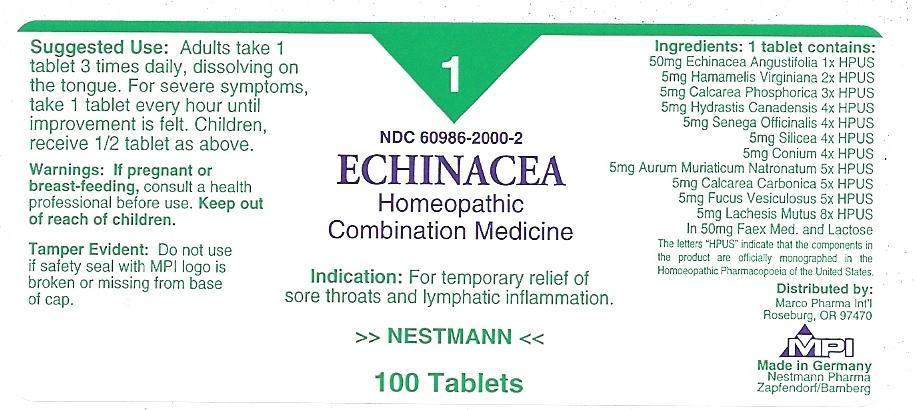 DRUG LABEL: ECHINACEA
NDC: 60986-2000 | Form: TABLET, ORALLY DISINTEGRATING
Manufacturer: Marco Pharma International LLC.
Category: homeopathic | Type: HUMAN OTC DRUG LABEL
Date: 20111205

ACTIVE INGREDIENTS: ECHINACEA ANGUSTIFOLIA 1 [hp_X]/1 1; HAMAMELIS VIRGINIANA ROOT BARK/STEM BARK 2 [hp_X]/1 1; TRIBASIC CALCIUM PHOSPHATE 3 [hp_X]/1 1; GOLDENSEAL 4 [hp_X]/1 1; POLYGALA SENEGA ROOT 4 [hp_X]/1 1; SILICON DIOXIDE 4 [hp_X]/1 1; CONIUM MACULATUM FLOWERING TOP 4 [hp_X]/1 1; SODIUM TETRACHLOROAURATE 5 [hp_X]/1 1; OYSTER SHELL CALCIUM CARBONATE, CRUDE 5 [hp_X]/1 1; FUCUS VESICULOSUS 5 [hp_X]/1 1; LACHESIS MUTA VENOM 8 [hp_X]/1 1
INACTIVE INGREDIENTS: SACCHAROMYCES CEREVISIAE; LACTOSE

Drug Facts

Active Ingredients

ECHINACEA ANGUSTIFOLIA 1XHPUS

HAMAMELIS VIRGINIANA 2XHPUS

CALCAREA PHOSPHORICA 3XHPUS

HYDRASTIS CANADENSIS 4XHPUS

SENEGA OFFICINALIS 4XHPUS

SILICEA 4XHPUS

CONIUM 4XHPUS

AURUM MURIATICUM NATRONATUM 5XHPUS

CALCAREA CARBONICA 5XHPUS

FUCUS VESICULOSUS 5XHPUS

LACHESIS MUTUS 8XHPUS

The letters HPUS indicates that the components in this product are officially monographed in the Homeopathic Pharmacopoeia of United Sates.

Purpose

FOR TEMPORARY RELIEF OF SORE THROATS AND LYMPHATIC INFLAMMATION.

Keep out of reach of children.

Suggested use

Error

Warnings

If pregnant or breast-feeding, consult a health professional before use.

DOSAGE AND ADMINISTRATION

(Read Suggested Use Section)

Inactive Ingredients

Faex Med. and Lactose

PACKAGE LABEL

MM1